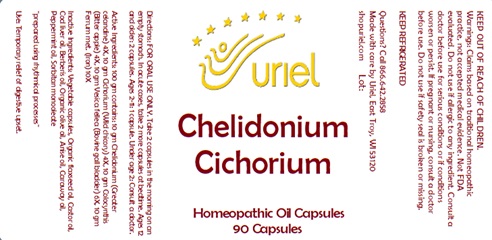 DRUG LABEL: Chelidonium Cichorium
NDC: 48951-3252 | Form: CAPSULE
Manufacturer: Uriel Pharmacy, Inc.
Category: homeopathic | Type: HUMAN OTC DRUG LABEL
Date: 20240304

ACTIVE INGREDIENTS: CITRULLUS COLOCYNTHIS FRUIT 4 [hp_X]/1 1; BOS TAURUS GALLBLADDER 6 [hp_X]/1 1; CICHORIUM INTYBUS WHOLE 4 [hp_X]/1 1; IRON 10 [hp_X]/1 1; CHELIDONIUM MAJUS 4 [hp_X]/1 1
INACTIVE INGREDIENTS: ANISE OIL; BERBERIS VULGARIS FRUIT; POWDERED CELLULOSE; LINSEED OIL; COD LIVER OIL; OLIVE OIL; PEPPERMINT OIL; SORBITAN MONOOLEATE; CARAWAY OIL; CASTOR OIL

Chelidonium Cichorium

INDICATIONS AND USAGE

Directions: FOR ORAL USE ONLY.

DOSAGE AND ADMINISTRATION

Take 2 capsules in the morning on an empty stomach. In acute cases, take 2 more capsules at bedtime. Ages 12 and older: 2 capsules. Ages 2-11: 1 capsule. Under age 2: Consult a doctor.

ACTIVE INGREDIENT

Active Ingredients: 100 gm contains: 10 gm Chelidonium (Greater celandine) 4X, 10 gm Cichorium (Wild chicory) 4X, 10 gm Colocynthis (Bitter apple) 4X, 10 gm Vesica fellea (Bovine gall bladder) 6X, 10 gm Ferrum met. (Iron) 10X

INACTIVE INGREDIENT

Inactive Ingredients: Vegetable capsules, Organic flaxseed oil, Castor oil, Cod liver oil, Berberis oil, Organic olive oil, Anise oil, Caraway oil, Peppermint oil, Sorbitan monooleate

"prepared using rhythmical processes"

PURPOSE

Use: Temporary relief of digestive upset.

KEEP OUT OF REACH OF CHILDREN.

WARNINGS

Warnings: Claims based on traditional homeopathic practice, not accepted medical evidence.
Not FDA evaluated. Do not use if allergic to any ingredient. Consult a doctor before use for
serious conditions or if conditions worsen or persist. If pregnant or nursing, consult a doctor before use. Do not use if safety seal is broken or missing.

KEEP REFRIGERATED

Questions? Call 866.642.2858
Made with care by Uriel, East Troy, WI 53120
shopuriel.com Lot: